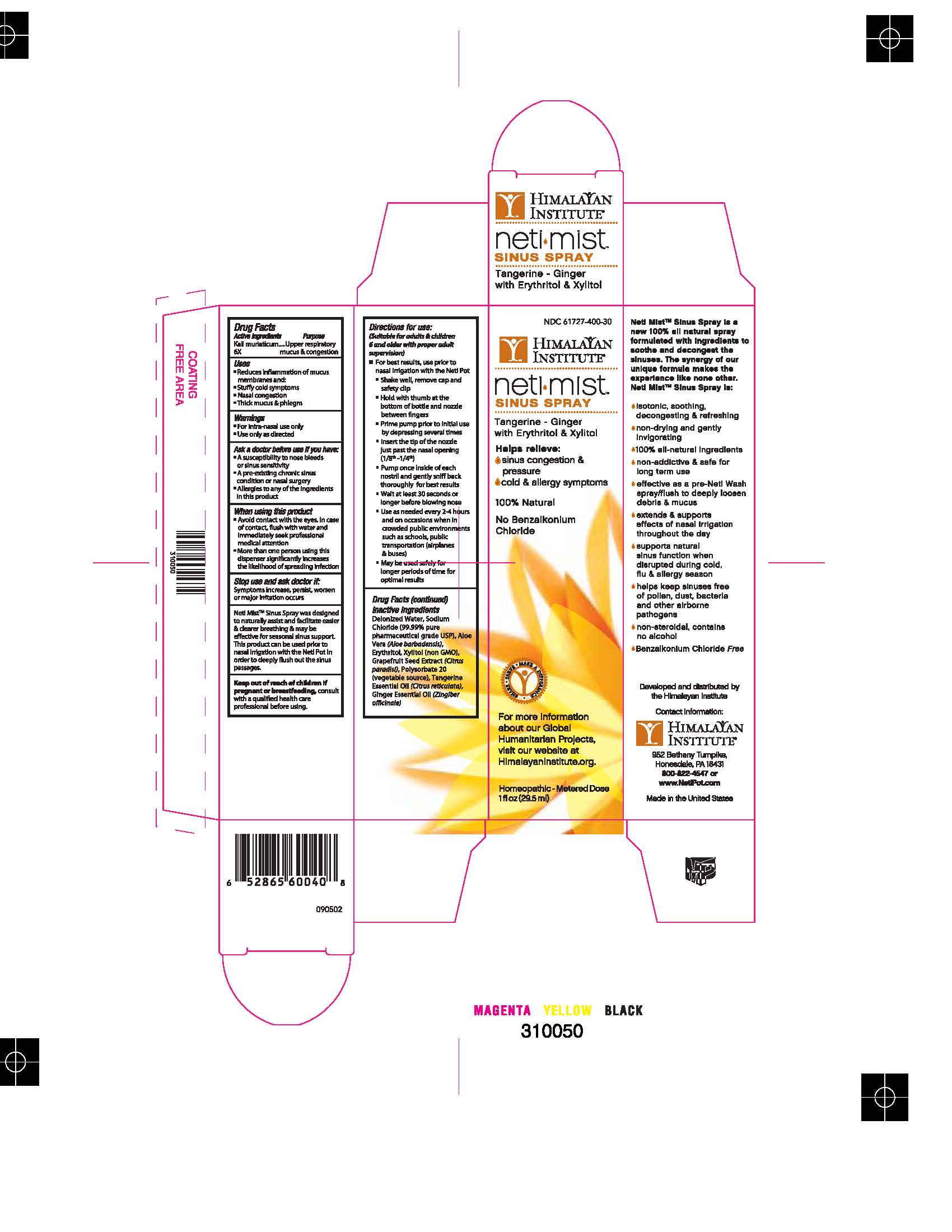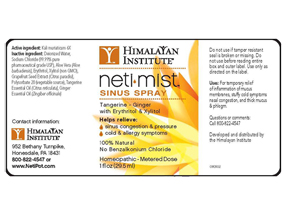 DRUG LABEL: Neti Mist Sinus Spray
NDC: 61727-400 | Form: LIQUID
Manufacturer: Homeocare Laboratories
Category: homeopathic | Type: HUMAN OTC DRUG LABEL
Date: 20111114

ACTIVE INGREDIENTS: POTASSIUM CHLORIDE 6 [hp_X]/29.5 mL
INACTIVE INGREDIENTS: ERYTHRITOL; XYLITOL; CITRUS PARADISI SEED; MANDARIN OIL; GINGER; WATER; POLYSORBATE 20 ; ALOE VERA LEAF

Active Ingredients:

ACTIVE INGREDIENT

Kali muriaticum 6x

Purpose:

Upper respiratory mucus and congestion

Keep out of reach of children if pregnant or breastfeeding, consult with a qualified health care professional before using.

Uses:

- Reduces inflammation of mucus
- Stuffy cold symptoms
- Nasal congestion
- Thick mucus and phlegm

Warnings:

*For Intra-nasal use only

*Use only as directed

Inactive Ingredients:

Deionized Water, Sodium Chloride (99.99% pure pharmaceutical grade USP), Aloe Vera (Aloe barbadensis), Erythritol, Xylitol (non GMO), Grapefruit Seed Extract (Citrus paradisi), Polysorbate 20 (vegetable source), Tangerine Essential Oil (Citrus reticulata), Ginger Essential Oil (Zingiber officinale).

Neti Mist Sinus Spray

NMSS

NetiMist Sinus Spray.jpg

NMSSBOX

BoxProof60040HIM1OZ000.jpg